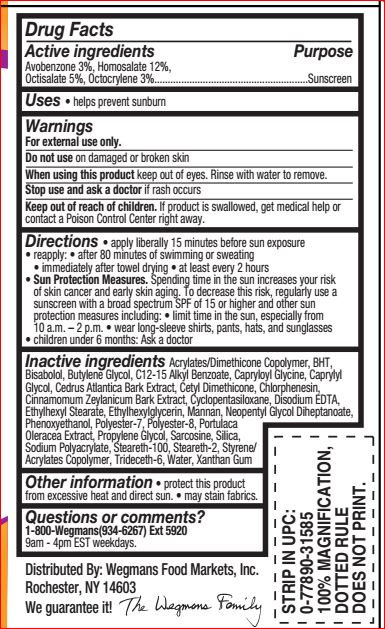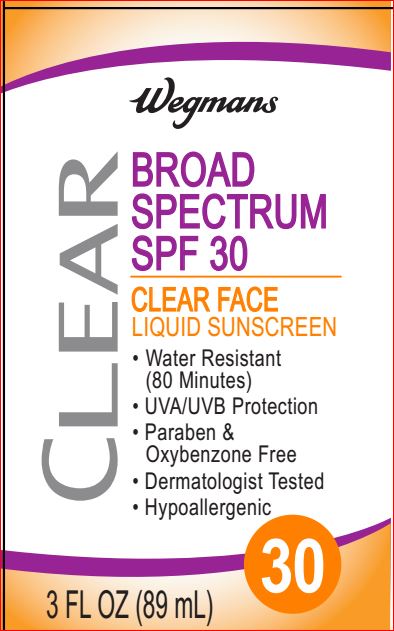 DRUG LABEL: Clear SPF 30 Face Sunscreen
NDC: 47124-451 | Form: LIQUID
Manufacturer: Wegman
Category: otc | Type: HUMAN OTC DRUG LABEL
Date: 20180109

ACTIVE INGREDIENTS: Avobenzone 3 g/100 mL; Homosalate 12 g/100 mL; Octisalate 5 g/100 mL; Octocrylene 3 g/100 mL
INACTIVE INGREDIENTS: BUTYLATED HYDROXYTOLUENE; LEVOMENOL; Butylene Glycol; ALKYL (C12-15) BENZOATE; Capryloyl Glycine; Caprylyl Glycol; CEDRUS ATLANTICA BARK; CINNAMON BARK OIL; CYCLOMETHICONE 5; EDETATE DISODIUM; Ethylhexyl Stearate; Ethylhexylglycerin; YEAST MANNAN; Neopentyl Glycol Diheptanoate; Phenoxyethanol; Polyester-7; Propylene Glycol; PURSLANE; Sarcosine; Steareth-2; Steareth-100; TRIDECETH-6 PHOSPHATE; Water; Xanthan Gum

Active ingredients Purpose

Avobenzone 3%, Homosalate 12%,
Octisalate 5%, Octocrylene 3%.........................................................Sunscreen

INDICATIONS AND USAGE

Uses • helps prevent sunburn

Warnings

For external use only
Do not use on damaged or broken skin
When using this product keep out of eyes. Rinse with water to remove.
Stop use and ask a doctor if rash occurs
Keep out of reach of children. If product is swallowed, get medical help or contact a Poison Control Center right away.

Directions

• apply liberally 15 minutes before sun exposure
• reapply: • after 80 minutes of swimming or sweating
• immediately after towel drying • at least every 2 hours
• Sun Protection Measures. Spending time in the sun
increases your risk of skin cancer and early skin aging.
To decrease this risk, regularly use a sunscreen with a
broad spectrum SPF of 15 or higher and other sun
protection measures including:
• limit time in the sun, especially from 10 a.m. – 2 p.m.
• wear long-sleeve shirts, pants, hats, and sunglasses
• children under 6 months: Ask a doctor

Inactive ingredients

Acrylates/Dimethicone Copolymer
BHT
Bisabolol
Butylene Glycol
C12-15 Alkyl Benzoate
Capryloyl Glycine
Caprylyl Glycol
Cedrus Atlantica Bark Extract
Cetyl Dimethicone
Chlorphenesin
Cinnamomum Zeylanicum Bark Extract
Cyclopentasiloxane
Disodium EDTA
Ethylhexyl Stearate
Ethylhexylglycerin
Mannan
Neopentyl Glycol Diheptanoate
Phenoxyethanol
Polyester-7
Polyester-8
Portulaca Oleracea Extract
Propylene Glycol
Sarcosine
Silica
Sodium Polyacrylate
Steareth-2
Steareth-100
Styrene/Acrylates Copolymer
Trideceth-6
Water
Xanthan Gum

Other information

• protect this product from excessive heat and direct sun • may stain fabrics.

Questions or comments?

1-800-Wegmans(934-6267) Ext 5920
9am - 4pm EST weekdays.